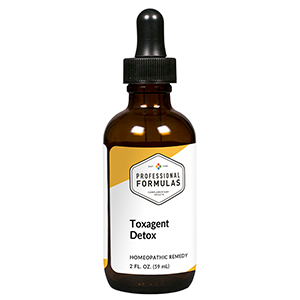 DRUG LABEL: Toxagent Detox
NDC: 63083-6035 | Form: LIQUID
Manufacturer: Professional Complementary Health Formulas
Category: homeopathic | Type: HUMAN OTC DRUG LABEL
Date: 20190815

ACTIVE INGREDIENTS: CHLORINE 12 [hp_X]/59 mL; CHLOROFORM 12 [hp_X]/59 mL; FLUORINE 12 [hp_X]/59 mL; METHANE 12 [hp_X]/59 mL; PHOSFOLAN 12 [hp_X]/59 mL; SULFUR 12 [hp_X]/59 mL; APIS MELLIFERA 12 [hp_X]/59 mL; ONION 30 [hp_X]/59 mL; AMMONIUM CATION 30 [hp_X]/59 mL; ARSENIC TRIOXIDE 30 [hp_X]/59 mL; DIEFFENBACHIA SEGUINE WHOLE 30 [hp_X]/59 mL; NITRIC ACID 30 [hp_X]/59 mL; FENSON 30 [hp_X]/59 mL; PROPANE 30 [hp_X]/59 mL; SULFURIC ACID 30 [hp_X]/59 mL; VERATRUM ALBUM ROOT 30 [hp_X]/59 mL; CALENDULA OFFICINALIS FLOWERING TOP 30 [hp_X]/59 mL; 2,3,7,8-TETRACHLORODIBENZO-P-DIOXIN 60 [hp_X]/59 mL; ACONITUM NAPELLUS WHOLE 200 [hp_X]/59 mL; ARNICA MONTANA WHOLE 200 [hp_X]/59 mL; BENZENE 200 [hp_X]/59 mL; HYDROGEN CYANIDE 200 [hp_X]/59 mL; POTASSIUM CYANIDE 200 [hp_X]/59 mL
INACTIVE INGREDIENTS: ALCOHOL; WATER

X35

ACTIVE INGREDIENTS

Chlorinum 12X
Chloroformum 12X
Fluorine 12X
Methane 12X
Phospholan 12X
Sulphur amine 12X
Apis mellifica 12X, 30X, 60X
Allium cepa 30X
Ammonium nitricum 30X
Arsenicum album 30X
Caladium seguinum 30X
Nitricum acidum 30X
PCBs 30X
Propane 30X
Sulphuricum acidum 30X
Veratrum album 30X
Calendula officinalis 30X, 60X, 100X
Dioxin 60X
Aconitum napellus 200X
Arnica montana 200X
Benzinum 200X
Hydrocyanicum acidum 200X
Kali cyanatum 200X

QUESTIONS

Professional Formulas

PO Box 2034 Lake Oswego, OR 97035

INDICATIONS

For the temporary relief of irritation of the nose, throat, eyes, or skin, occasional headache, shortness of breath, or fatigue due to sensitivity to or exposure to industrial processes or environmental contaminants.*

PURPOSE

*Claims based on traditional homeopathic practice, not accepted medical evidence. Not FDA evaluated.

WARNINGS

In case of overdose, get medical help or contact a poison control center right away.

Keep out of the reach of children.

PREGNANCY OR BREAST FEEDING

If pregnant or breastfeeding, ask a healthcare professional before use.

DIRECTIONS

Place drops under tongue 30 minutes before/after meals. Adults and children 12 years and over: Take 10 drops up to 3 times per day. Consult a physician for use in children under 12 years of age.

OTHER INFORMATION

Tamper resistant. If seal is broken, do not use. After opening, close container tightly and store at room temperature away from heat.

INACTIVE INGREDIENTS

20% ethanol, purified water.

LABEL

Est 1985

Professional Formulas

Complementary Health

Toxagent Detox

Homeopathic Remedy

2 FL. OZ. (59 mL)